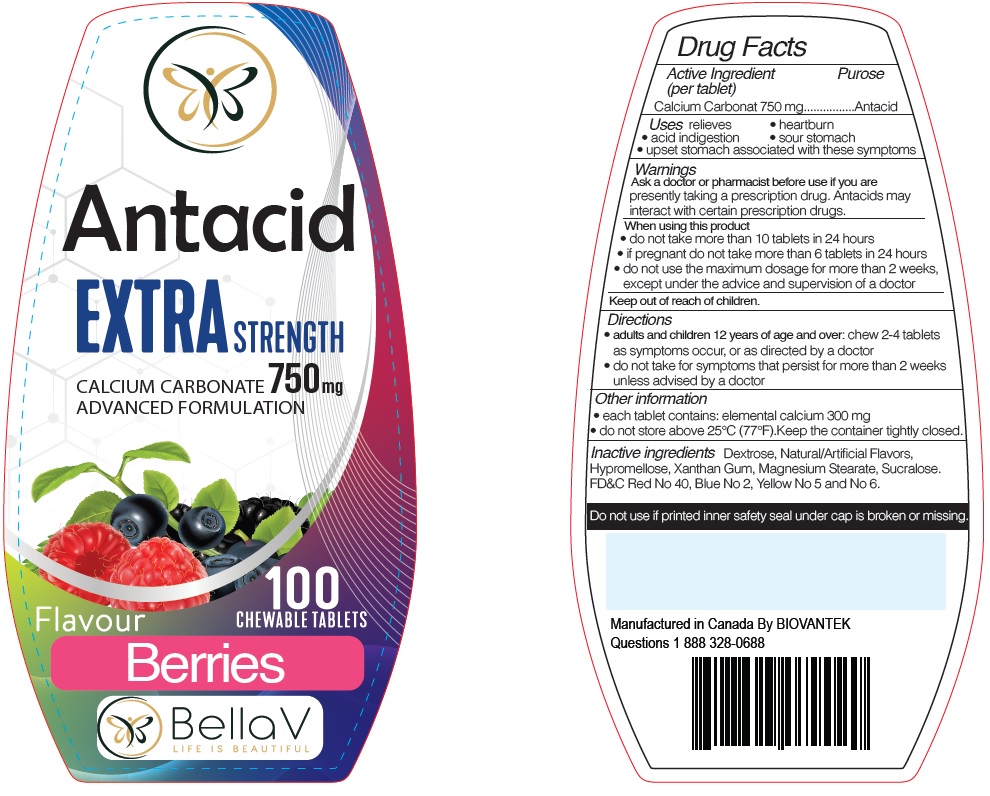 DRUG LABEL: Bella V Antacid Extra Strength Berries Flavor
NDC: 83422-000 | Form: TABLET
Manufacturer: Biovantek
Category: otc | Type: HUMAN OTC DRUG LABEL
Date: 20250116

ACTIVE INGREDIENTS: CALCIUM CARBONATE 750 mg/1 1
INACTIVE INGREDIENTS: DEXTROSE; HYPROMELLOSE, UNSPECIFIED; XANTHAN GUM; MAGNESIUM STEARATE; SUCRALOSE; FD&C RED NO. 40; FD&C BLUE NO. 2; FD&C YELLOW NO. 5; FD&C YELLOW NO. 6

Bella V Antacid Extra Strength Berries Flavor

Active Ingredient per tablet)

Calcium Carbonat 750 mg

Purose

Antacid

Uses

relieves • heartburn • acid indigestion • sour stomach • upset stomach associated with these symptoms

Warnings

Ask a doctor or pharmacist before use

if you are presently taking a prescription drug. Antacids may interact with certain prescription drugs.

When using this product

• do not take more than 10 tablets in 24 hours
• if pregnant do not take more than 6 tablets in 24 hours
• do not use the maximum dosage for more than 2 weeks, except under the advice and supervision of a doctor

Directions

• adults and children 12 years of age and over: chew 2-4 tablets as symptoms occur, or as directed by a doctor
• do not take for symptoms that persist for more than 2 weeks unless advised by a doctor

Other information

• each tablet contains: elemental calcium 300 mg
• do not store above 25°C (77°F).Keep the container tightly closed.

Inactive ingredients

Dextrose, Natural/Artificial Flavors, Hypromellose, Xanthan Gum, Magnesium Stearate, Sucralose. FD&C Red No 40, Blue No 2, Yellow No 5 and No 6.